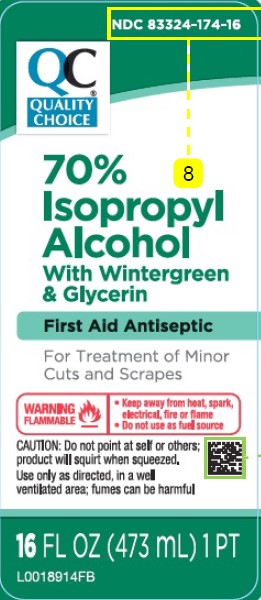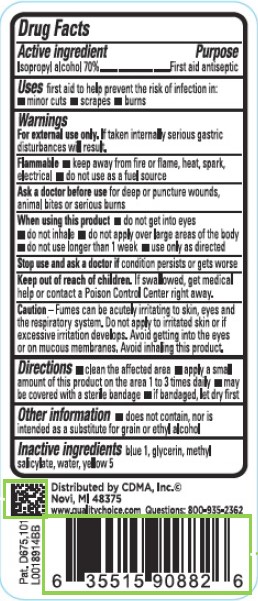 DRUG LABEL: Isopropyl Alcohol
NDC: 83324-174 | Form: LIQUID
Manufacturer: Chain Drug Marketing Association
Category: otc | Type: HUMAN OTC DRUG LABEL
Date: 20260227

ACTIVE INGREDIENTS: ISOPROPYL ALCOHOL 70 mL/100 mL
INACTIVE INGREDIENTS: FD&C BLUE NO. 1; GLYCERIN; METHYL SALICYLATE; WATER; FD&C YELLOW NO. 5

Quality Choice 845.003/845AE
70% IPA with Wintergreen

Active ingredient

Isopropyl alcohol 70%

Purpose

First aid antiseptic

Use

first aid to help prevent the risk of infection in:

- minor cuts
- scrapes
- burns

Warnings

For external use only.If taken internally serious gastric disturbances will result.

Flammable

- keep away from fire or flame, heat, spark, electrical
- do not use as a fuel source

Ask a doctor before use

for deep or puncture wounds, animal bites or serious burns

When using this product

- do not get into eyes
- do not inhale
- do not apply over large areas of the body
- do not use longer than 1 week
- use only as directed

Stop use and ask a doctor if

condition persists or gets worse

Keep out of reach of children.

If swallowed, get medical help or contact a Poison Control Center right away.

Caution

Fumes can be acutely irritating to skin, eyes and the respiratory system. Do not apply to irritated skin or if excessive irritation develops. Avoid gettting into the eyes or on mucous membranes. Avoid inhaling this product.

Directions

- clean the affected area
- apply a small amount of this product on the area 1 to 3 times daily
- may be covered with a sterile bandage
- if bandaged, let dry first

Other information

- does not contain, nor is intended as a substitute for grain or ethyl alcohol

Inactive ingredients

blue 1, glycerin, methyl salicylate, water, yellow 5

Adverse reaction

Distributed by CDMA, Inc. ©

Novi, MI 48375

www.qualitychoice.com Questions: 800-935-2362

Pat. D675,101

Principal display panel

NDC 83324-174-16

QC®

QUALITY

CHOICE

70%

Isopropyl

Alcohol

With Wintergreen

& Glycerin

First Aid Antiseptic

For Treatment of Minor

Cuts and Scranpes

WARNING

FLAMMABLE

- Keep away from heat, spark, electrical, fire or flame
- Do not use as fuel source

CAUTION: Do not point at self or others; product will squirt when squeezed.

Use only as directed, in a well ventiliated area: fumes can be harmful.

16 fl oz (473 mL)